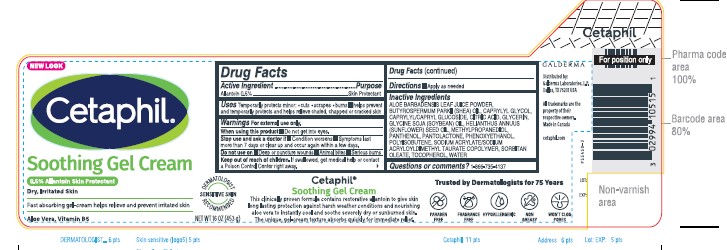 DRUG LABEL: Cetaphil Soothing Gel Cream
NDC: 0299-4105 | Form: CREAM
Manufacturer: Galderma Laboratories, L.P.
Category: otc | Type: HUMAN OTC DRUG LABEL
Date: 20231211

ACTIVE INGREDIENTS: Allantoin 5 mg/1 g
INACTIVE INGREDIENTS: Aloe Vera Leaf; Sheanut Oil; Caprylyl Glycol; Caprylyl/Capryl Oligoglucoside; Citric Acid Monohydrate; Glycerin; Soybean Oil; Sunflower Oil; Methylpropanediol; Panthenol; Pantolactone, (R)-; Phenoxyethanol; Polyisobutylene (1000 Mw); Sodium Acrylate/Sodium Acryloyldimethyltaurate Copolymer (4000000 Mw); Tocopherol; Water; Sorbitan Monooleate

Drug Facts

Active ingredients......Purpose

Allantoin 0.5%......Skin Protectant

Uses

Temporarily protects minor: ●cuts
●scrapes ●burns ■helps prevent and temporarily
protects and helps relieve chafed, chapped or
cracked skin

Warnings

For external use only.

When using this product ■ Do not get into eyes.

Stop use and ask a Doctor if ● condition worsens ● symptoms last more than 7 days or clear up and occur again within a few days.

Do not use on ■Deep or puncture wounds
■Animal bites ■Serious burns

Keep out of reach of children. If swallowed, get medical help or contact a Poison Control Center right away.

Directions

■Apply as needed

Inactive Ingredients

ALOE BARBADENSIS LEAF JUICE POWDER, BUTYROSPERMUM PARKII (SHEA) OIL, CAPRYLYL GLYCOL, CAPRYLYL/CAPRYL GLUCOSIDE, CITRIC ACID, GLYCERIN, GLYCINE SOJA (SOYBEAN) OIL, HELIANTHUS ANNUUS (SUNFLOWER) SEED OIL, METHYLPROPANEDIOL, PANTHENOL, PANTOLACTONE, PHENOXYETHANOL, POLYISOBUTENE, SODIUM ACRYLATE/SODIUM ACRYLOYLDIMETHYL TAURATE COPOLYMER, SORBITAN OLEATE, TOCOPHEROL, WATER

Questions or comments?

1-866-735-4137

PRINCIPLE DISPLAY PANEL - 16 OZ jar

NEW LOOK

Cetaphil®

Soothing Gel Cream
0.5% Allantoin Skin Protectant

Dry, Irritated Skin

Fast absorbing gel-cream
helps relieves and prevent irritated skin.

Aloe Vera, Vitamin B5
Dermatologist Recommended
Sensitive Skin

NET WT 16 OZ (453 g)

Distributed By:
Galderma Laboratories, L.P.
Dallas, TX 75201 USA

All trademarks are the property of their respective owners.
Made in Canada.
cetaphil.com
P55450-3